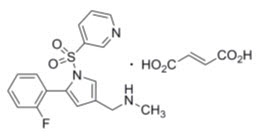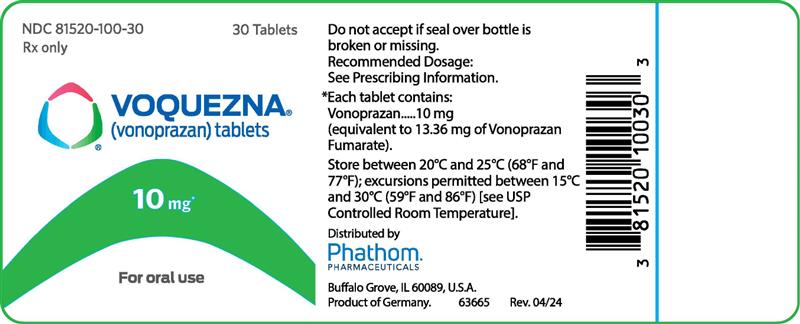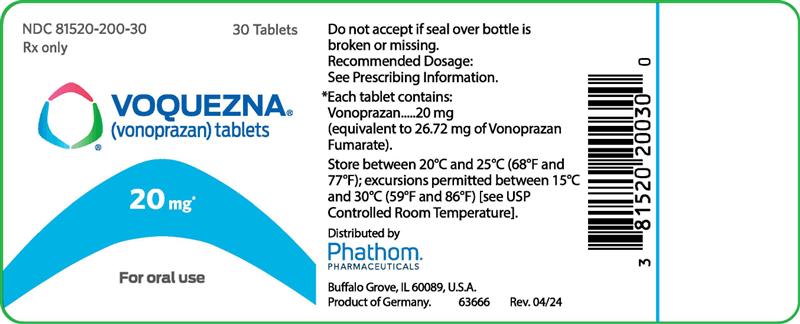 DRUG LABEL: VOQUEZNA
NDC: 81520-100 | Form: TABLET
Manufacturer: Phathom Pharmaceuticals Inc.
Category: prescription | Type: HUMAN PRESCRIPTION DRUG LABEL
Date: 20251118

ACTIVE INGREDIENTS: vonoprazan fumarate 13.36 mg/1 1
INACTIVE INGREDIENTS: Mannitol; Microcrystalline Cellulose; Hydroxypropyl Cellulose, Unspecified; Fumaric Acid; Ascorbic acid; Croscarmellose sodium; Magnesium Stearate; Hypromellose, unspecified; Polyethylene Glycol 8000; Titanium Dioxide; Ferric Oxide Yellow

HIGHLIGHTS OF PRESCRIBING INFORMATION

These highlights do not include all the information needed to use VOQUEZNA® safely and effectively. See full prescribing information for VOQUEZNA.
VOQUEZNA (vonoprazan) tablets, for oral use
Initial U.S. Approval: 2022

1 INDICATIONS AND USAGE

VOQUEZNA is a potassium-competitive acid blocker indicated:

- for healing of all grades of erosive esophagitis and relief of heartburn associated with erosive esophagitis in adults. (1)
- to maintain healing of all grades of erosive esophagitis and relief of heartburn associated with erosive esophagitis in adults. (1)
- for the relief of heartburn associated with non-erosive gastroesophageal reflux disease in adults. (1)
- in combination with amoxicillin and clarithromycin for the treatment of Helicobacter pylori (H. pylori) infection in adults. (1)
- in combination with amoxicillin for the treatment of H. pylori infection in adults. (1)

2 DOSAGE AND ADMINISTRATION

Recommended Dosage:

- Healing of Erosive Esophagitis: 20 mg once daily for 8 weeks. (2.1)
- Maintenance of Healed Erosive Esophagitis: 10 mg once daily for up to 6 months. (2.1)
- Relief of Heartburn Associated with Non-Erosive Gastroesophageal Reflux Disease: 10 mg once daily for 4 weeks. (2.1)
- Treatment of H. pylori Infection: see full prescribing information. (2.1)
- See also full prescribing information for the recommended dosage by indication for patients with renal or hepatic impairment. (2.2, 2.3)

Administration Instructions:

- Take with or without food. (2.4)
- Swallow whole; do not chew or crush. (2.4)

3 DOSAGE FORMS AND STRENGTHS

Tablets: 10 mg and 20 mg of vonoprazan. (3)

4 CONTRAINDICATIONS

- Known hypersensitivity to vonoprazan or any component of VOQUEZNA. (4)
- Rilpivirine-containing products. (4, 7)

5 WARNINGS AND PRECAUTIONS

- Gastric Malignancy: Symptomatic response to treatment does not preclude the presence of gastric malignancy; consider additional follow-up and diagnostic testing. (5.1)
- Acute Tubulointerstitial Nephritis: Discontinue treatment and evaluate patients. (5.2)
- Clostridioides difficile-Associated Diarrhea (CDAD): May be associated with an increased risk; use the shortest duration of treatment appropriate to the condition. (5.3)
- Bone Fracture, including Osteoporosis-related Fracture: Use the shortest duration of treatment appropriate to the condition. (5.4)
- Severe Cutaneous Adverse Reactions: Discontinue at the first signs or symptoms of severe cutaneous adverse reactions or other signs of hypersensitivity and consider further evaluation. (5.5)
- Vitamin B12 (Cobalamin) Deficiency: Long-term use may lead to malabsorption or deficiency; consider further workup if clinical symptoms are present. (5.6)
- Hypomagnesemia and Mineral Metabolism: Hypomagnesemia may lead to hypocalcemia and/or hypokalemia. Consider monitoring magnesium and calcium levels in at-risk patients, or if there is concomitant use of digoxin or other drugs that cause hypomagnesemia. (5.7)
- Interactions with Investigations for Neuroendocrine Tumors: Increased chromogranin A (CgA) levels may interfere with diagnostic investigations; temporarily stop VOQUEZNA at least 4 weeks before assessing CgA levels. (5.8, 7)
- Fundic Gland Polyps: Risk increases with long-term use; use the shortest duration of treatment appropriate to the condition. (5.9)

6 ADVERSE REACTIONS

Most common adverse reactions in VOQUEZNA-treated patients are:

- Healing of Erosive Esophagitis (≥2%): gastritis, diarrhea, abdominal distension, abdominal pain, and nausea. (6.1)
- Maintenance of Healed Erosive Esophagitis (≥3%): gastritis, abdominal pain, dyspepsia, hypertension, and urinary tract infection. (6.1)
- Relief of Heartburn Associated with Non-Erosive Gastroesophageal Reflux Disease (≥2%): abdominal pain, constipation, diarrhea, nausea, and urinary tract infection. (6.1)
- Treatment of H. pylori Infection (≥2%): diarrhea, dysgeusia, vulvovaginal candidiasis, abdominal pain, headache, hypertension, and nasopharyngitis. (6.1)

To report SUSPECTED ADVERSE REACTIONS, contact Phathom Pharmaceuticals, Inc. at toll-free phone 1-888-775-7428 or FDA at 1-800-FDA-1088 or www.fda.gov/medwatch.

7 DRUG INTERACTIONS

See full prescribing information for a list of clinically important drug interactions. (7)

FULL PRESCRIBING INFORMATION

1 INDICATIONS AND USAGE

VOQUEZNA is indicated:

- for healing of all grades of erosive esophagitis and relief of heartburn associated with erosive esophagitis in adults.
- to maintain healing of all grades of erosive esophagitis and relief of heartburn associated with erosive esophagitis in adults.
- for the relief of heartburn associated with non-erosive gastroesophageal reflux disease in adults.
- in combination with amoxicillin and clarithromycin for the treatment of Helicobacter pylori (H. pylori) infection in adults.
- in combination with amoxicillin for the treatment of H. pylori infection in adults.

2 DOSAGE AND ADMINISTRATION

2.1 Recommended Dosage

Healing of Erosive Esophagitis

- The recommended adult oral dosage is VOQUEZNA 20 mg once daily for 8 weeks for the treatment of healing of erosive esophagitis and relief of associated heartburn.

Maintenance of Healed Erosive Esophagitis

- The recommended adult oral dosage is VOQUEZNA 10 mg once daily for up to 6 months for the maintenance of healed erosive esophagitis and relief of associated heartburn.

Relief of Heartburn Associated with Non-Erosive Gastroesophageal Reflux Disease

- The recommended adult oral dosage is VOQUEZNA 10 mg once daily for 4 weeks.

Treatment of H. pylori Infection

- Triple Therapy: The recommended adult oral dosage is VOQUEZNA 20 mg plus amoxicillin 1,000 mg plus clarithromycin 500 mg, each given twice daily (in the morning and evening, 12 hours apart) for 14 days.
- Dual Therapy: The recommended adult oral dose is VOQUEZNA 20 mg given twice daily (in the morning and evening) plus amoxicillin 1,000 mg three times daily (in the morning, mid-day, and evening) for 14 days.
- Also refer to the amoxicillin and clarithromycin full prescribing information.

2.2 Recommended Dosage in Patients with Renal Impairment

Healing of Erosive Esophagitis

The recommended dosage of VOQUEZNA in adult patients with renal impairment is described in Table 1 below [see Use in Specific Populations (8.6) and Clinical Pharmacology (12.3)].

Table 1: Recommended VOQUEZNA Dosage in Patients with Renal Impairment: Healing of Erosive Esophagitis
Estimated glomerular filtration rate (GFR) | Recommended Dosage
30 mL/minute or greater | 20 mg once daily
Less than 30 mL/minute | 10 mg once daily

Maintenance of Healed Erosive Esophagitis or Relief of Heartburn Associated with Non-Erosive Gastroesophageal Reflux Disease

The recommended dosage of VOQUEZNA in adult patients with renal impairment is the same as for adult patients with normal renal function [see Dosage and Administration (2.1)].

Treatment of H. pylori Infection

The recommended dosage of VOQUEZNA in adult patients with renal impairment is described in Table 2 below [see Use in Specific Populations (8.6) and Clinical Pharmacology (12.3)].

Table 2: Recommended VOQUEZNA Dosage in Patients with Renal Impairment: Treatment of H. pylori Infection [Also refer to the Dosage and Administration section of the amoxicillin and clarithromycin prescribing information for dosage recommendations in patients with renal impairment.]
Estimated GFR | Recommended Dosage
30 mL/minute or greater | 20 mg twice daily
Less than 30 mL/minute | Use is not recommended

2.3 Recommended Dosage in Patients with Hepatic Impairment

Healing of Erosive Esophagitis

The recommended dosage of VOQUEZNA in adult patients with hepatic impairment is described in Table 3 below [see Use in Specific Populations (8.7) and Clinical Pharmacology (12.3)].

Table 3: Recommended VOQUEZNA Dosage in Patients with Hepatic Impairment: Healing of Erosive Esophagitis
Classification | Recommended Dosage
Child-Pugh Class A | 20 mg once daily
Child-Pugh Class B | 10 mg once daily
Child-Pugh Class C | 10 mg once daily

Maintenance of Healed Erosive Esophagitis or Relief of Heartburn Associated with Non-Erosive Gastroesophageal Reflux Disease

The recommended dosage of VOQUEZNA in adult patients with hepatic impairment is the same as for patients with normal hepatic function [see Dosage and Administration (2.1)].

Treatment of H. pylori Infection

The recommended dosage of VOQUEZNA in adult patients with hepatic impairment is described in Table 4 below [see Use in Specific Populations (8.7) and Clinical Pharmacology (12.3)].

Table 4: Recommended VOQUEZNA Dosage in Patients with Hepatic Impairment: Treatment of H. pylori Infection
Classification | Recommended Dosage
Child-Pugh Class A | 20 mg twice daily
Child-Pugh Class B | Use is not recommended
Child-Pugh Class C | Use is not recommended

2.4 Administration Instructions

- Take VOQUEZNA with or without food [see Clinical Pharmacology (12.3)].
- Swallow VOQUEZNA tablets whole; do not chew or crush the tablet.
- Missed doses:
  - For the healing or maintenance of healed erosive esophagitis, or the relief of heartburn associated with non-erosive gastroesophageal reflux disease: If a dose is missed, administer VOQUEZNA as soon as possible within 12 hours after the missed dose. If more than 12 hours have passed, skip the missed dose and administer the next dose at the regularly scheduled time.
  - For the treatment of H. pylori infection: If a dose is missed, administer VOQUEZNA as soon as possible within 4 hours after the missed dose. If more than 4 hours have passed, skip the missed dose and administer the next dose at the regularly scheduled time. Continue the normal dosing schedule until the treatment is completed.

3 DOSAGE FORMS AND STRENGTHS

Tablets:

- 10 mg of vonoprazan: pale yellow, oval, film-coated tablets debossed V10 on one side and plain on the other side.
- 20 mg of vonoprazan: pale red, oval, film-coated tablets debossed V20 on one side and plain on the other side.

4 CONTRAINDICATIONS

- VOQUEZNA is contraindicated in patients with a known hypersensitivity to vonoprazan or any component of VOQUEZNA. Reactions have included anaphylactic shock [see Adverse Reactions (6.2) and Description (11)].
- VOQUEZNA is contraindicated with rilpivirine-containing products [see Drug Interactions (7)].
- For information about contraindications of antibacterial agents (clarithromycin and amoxicillin) indicated in combination with VOQUEZNA, refer to the Contraindications section of the corresponding prescribing information.

5 WARNINGS AND PRECAUTIONS

5.1 Presence of Gastric Malignancy

In adults, symptomatic response to therapy with VOQUEZNA does not preclude the presence of gastric malignancy. Consider additional follow-up and diagnostic testing in patients who have a suboptimal response or an early symptomatic relapse after completing treatment with VOQUEZNA. In older patients, also consider endoscopy.

5.2 Acute Tubulointerstitial Nephritis

Acute tubulointerstitial nephritis (TIN) has been reported with VOQUEZNA [see Adverse Reactions (6.1)]. If suspected, discontinue VOQUEZNA and evaluate patients with suspected acute TIN.

5.3 Clostridioides difficile-Associated Diarrhea

Published observational studies suggest that proton pump inhibitors (PPIs) may be associated with an increased risk of Clostridioides difficile-associated diarrhea (CDAD), especially in hospitalized patients. VOQUEZNA, another drug that blocks the proton pump to inhibit gastric acid production, may also increase the risk of CDAD. Consider CDAD in patients with diarrhea that does not improve [see Adverse Reactions (6.2)]. Use the shortest duration of VOQUEZNA appropriate to the condition being treated.

CDAD has been reported with use of nearly all antibacterial agents. For more information specific to antibacterial agents (clarithromycin and amoxicillin) indicated for use in combination with VOQUEZNA, refer to the Warnings and Precautions section of the corresponding prescribing information.

5.4 Bone Fracture

Several published observational studies suggest that PPI therapy may be associated with an increased risk for osteoporosis-related fractures of the hip, wrist, or spine. The risk of fracture was increased in patients who received high-dose, defined as multiple daily doses, and long-term therapy (a year or longer). Bone fracture, including osteoporosis-related fracture, has also been reported with vonoprazan. Use the shortest duration of VOQUEZNA appropriate to the condition being treated [see Dosage and Administration (2.1)]. Patients at risk for osteoporosis-related fractures should be managed according to the established treatment guidelines.

5.5 Severe Cutaneous Adverse Reactions

Severe cutaneous adverse reactions, including Stevens-Johnson syndrome (SJS) and toxic epidermal necrolysis (TEN) have been reported with VOQUEZNA [see Adverse Reactions (6.2)].

Discontinue VOQUEZNA at the first signs or symptoms of severe cutaneous adverse reactions or other signs of hypersensitivity and consider further evaluation.

5.6 Vitamin B12 (Cobalamin) Deficiency

Long-term use of acid-suppressing drugs can lead to malabsorption of Vitamin B12 caused by hypo- or achlorhydria. Vitamin B12 deficiency has been reported postmarketing with vonoprazan [see Adverse Reactions (6.2)]. If clinical symptoms consistent with Vitamin B12 deficiency are observed in patients treated with VOQUEZNA consider further workup.

5.7 Hypomagnesemia and Mineral Metabolism

Hypomagnesemia has been reported postmarketing with vonoprazan [see Adverse Reactions (6.2)]. Hypomagnesemia may lead to hypocalcemia and/or hypokalemia and may exacerbate underlying hypocalcemia in at-risk patients.

Consider monitoring magnesium levels prior to initiation of VOQUEZNA and periodically in patients expected to be on prolonged treatment, in patients taking drugs that may have increased toxicity in the presence of hypomagnesemia (e.g., digoxin), or drugs that may cause hypomagnesemia (e.g., diuretics). Treatment of hypomagnesemia may require magnesium replacement and discontinuation of VOQUEZNA.

Consider monitoring magnesium and calcium levels prior to initiation of VOQUEZNA and periodically while on treatment in patients with a preexisting risk of hypocalcemia (e.g., hypoparathyroidism). Supplement with magnesium and/or calcium, as necessary. If hypocalcemia is refractory to treatment, consider discontinuing VOQUEZNA.

5.8 Interactions with Diagnostic Investigations for Neuroendocrine Tumors

Serum chromogranin A (CgA) levels increase secondary to drug-induced decreases in gastric acidity. The increased CgA level may cause false positive results in diagnostic investigations for neuroendocrine tumors. Temporarily discontinue VOQUEZNA treatment at least 4 weeks before assessing CgA levels and consider repeating the test if initial CgA levels are high. If serial tests are performed (e.g., for monitoring), the same commercial laboratory should be used for testing, as reference ranges between tests may vary [see Drug Interactions (7) and Clinical Pharmacology (12.2)].

5.9 Fundic Gland Polyps

Use of VOQUEZNA is associated with a risk of fundic gland polyps that increases with long-term use, especially beyond one year. Fundic gland polyps have been reported with vonoprazan in clinical trials and postmarketing use with PPIs. Most patients who developed fundic gland polyps were asymptomatic and fundic gland polyps were identified incidentally on endoscopy. Use the shortest duration of VOQUEZNA appropriate to the condition being treated [see Dosage and Administration (2.1)].

6 ADVERSE REACTIONS

The following serious adverse reactions are described elsewhere in labeling:

- Acute Tubulointerstitial Nephritis [see Warnings and Precautions (5.2)]
- Clostridioides difficile-Associated Diarrhea [see Warnings and Precautions (5.3)]
- Bone Fracture [see Warnings and Precautions (5.4)]
- Severe Cutaneous Adverse Reactions [see Warnings and Precautions (5.5)]
- Vitamin B12 (Cobalamin) Deficiency [see Warnings and Precautions (5.6)]
- Hypomagnesemia and Mineral Metabolism [see Warnings and Precautions (5.7)]
- Fundic Gland Polyps [see Warnings and Precautions (5.9)]

6.1 Clinical Trials Experience

Because clinical trials are conducted under widely varying conditions, adverse reaction rates observed in the clinical trials of a drug cannot be directly compared to rates in the clinical trials of another drug and may not reflect the rates observed in practice.

Healing of Erosive Esophagitis and Maintenance of Healed Erosive Esophagitis

The safety of VOQUEZNA was evaluated in a randomized, active-controlled, double-blind two phase trial for the healing of erosive esophagitis (2 to 8 weeks) and maintenance of healed erosive esophagitis (through 24 weeks) conducted in the United States and Europe [see Clinical Studies (14.1), (14.2)].

Adverse reactions reported in at least 2% of patients in the VOQUEZNA 20 mg once daily arm in the healing phase are presented in Table 5.

Table 5: Adverse Reactions [Reported in at least 2% of patients in the VOQUEZNA arm.] in a Clinical Trial of Adult Patients with All Grades of Erosive Esophagitis [The trial was not designed to support comparative claims for VOQUEZNA for the adverse reactions reported in this table.] (2 to 8 Week Healing Phase)
Adverse Reactions | VOQUEZNA 20 mg Once Daily N=514 % | Lansoprazole 30 mg Once Daily N=510 %
Gastritis [Represents a grouped term and includes related terms.] | 3 | 2
Diarrhea | 2 | 3
Abdominal distension | 2 | 1
Abdominal pain | 2 | 1
Nausea | 2 | 1

Adverse reactions reported in at least 3% of patients in the VOQUEZNA 10 mg once daily arm of the maintenance phase are shown in Table 6.

Table 6: Adverse Reactions [Reported in at least 3% of patients in the VOQUEZNA arm.] in a Clinical Trial of Adult Patients with All Grades of Erosive Esophagitis [The trial was not designed to support comparative claims for VOQUEZNA for the adverse reactions reported in this table.] (24 Week Maintenance Phase)
Adverse Reactions | VOQUEZNA 10 mg Once Daily N=296 % | Lansoprazole 15 mg Once Daily N=297 %
Gastritis [Represents a grouped term and includes related terms.] | 6 | 3
Abdominal pain | 4 | 2
Dyspepsia | 4 | 3
Hypertension | 3 | 2
Urinary tract infection | 3 | 2

COVID-19

COVID-19 was reported in the healing phase in 11 (2%) VOQUEZNA-treated patients and 9 (2%) lansoprazole-treated patients, and in the maintenance phase in 18 (6%) VOQUEZNA-treated patients and 20 (7%) lansoprazole-treated patients.

Other Clinical Trials of Erosive Esophagitis

Adverse reactions reported in the United States trial were similar to those reported in 4 additional randomized, active-controlled, double-blind studies of vonoprazan compared to lansoprazole conducted outside of the United States (two 8-week trials of healing of erosive esophagitis and two 24-week maintenance of healed erosive esophagitis trials).

Relief of Heartburn Associated with Non-Erosive Gastroesophageal Reflux Disease

The safety of VOQUEZNA 10 mg once daily for the relief of heartburn associated with non-erosive gastroesophageal reflux disease was evaluated in a randomized, placebo-controlled, double-blind, four-week trial with a 20-week extension phase conducted in the United States [see Clinical Studies (14.3)]. Patients initially randomized to placebo in the 4-week placebo-controlled phase were re-randomized to VOQUEZNA 10 mg once daily or a higher dosage of VOQUEZNA for 20 weeks in the extension phase.

Adverse reactions reported in at least 2% of patients in the VOQUEZNA 10 mg once daily arm in the 4-week placebo-controlled phase are presented in Table 7.

Table 7: Adverse Reactions [Reported in at least 2% of patients in the VOQUEZNA arm.] in a Clinical Trial of Adult Patients with Non-Erosive Gastroesophageal Reflux Disease (4-week Placebo-Controlled Phase)
Adverse Reactions | VOQUEZNA 10 mg Once Daily N=259 % | Placebo Once Daily N=256 %
Abdominal pain [Represents a grouped term and includes related terms.] | 2 | 2
Constipation | 2 | 1
Diarrhea | 2 | 1
Nausea | 2 | <1
Urinary tract infection | 2 | 1

Other adverse reactions: Upper respiratory tract infection (4%) and sinusitis (3%) were reported in patients who received VOQUEZNA 10 mg once daily in the 20-week extension phase.

COVID-19

COVID-19 was reported in the 4-week placebo-controlled phase in 3 (1%) patients who received VOQUEZNA 10 mg once daily and 3 (1%) patients who received placebo, and in 24 (7%) patients who received VOQUEZNA 10 mg once daily in the 20-week extension phase.

Less Common Adverse Reactions

Adverse reactions reported in 1% or less of VOQUEZNA-treated patients for the healing or maintenance of healed erosive esophagitis or for the relief of heartburn associated with non-erosive gastroesophageal reflux disease in the United States trials are:

Blood and lymphatic system disorders: anemia, lymphocytosis

Cardiac disorders: tachycardia

Ear and labyrinth disorders: vertigo

Gastrointestinal disorders: duodenal polyp, dry mouth, dysphagia, eructation, flatulence, gastric polyps, vomiting

General disorders and administrative site conditions: asthenia, peripheral edema

Investigations: increased liver enzymes

Metabolism and nutritional disorders: diabetes mellitus

Musculoskeletal system: bone fracture

Nervous system disorders: dizziness, headache, syncope

Psychiatric disorders: depression, insomnia

Renal and urinary disorders: tubulointerstitial nephritis

Skin and subcutaneous tissue disorders: eczema, rash, urticaria

Treatment of H. pylori Infection

The safety of VOQUEZNA, amoxicillin and clarithromycin was evaluated in 675 adult patients (aged 20 to 82 years) in clinical trials in the United States, Europe, and Japan, and VOQUEZNA and amoxicillin was evaluated in 348 adult patients (aged 20 to 80 years) in a clinical trial in the United States and Europe. All of the patients were screened and found to be positive for H. pylori infection.

The safety of VOQUEZNA, amoxicillin, and clarithromycin (triple therapy) and VOQUEZNA and amoxicillin (dual therapy) was evaluated in a randomized, controlled, double-blind (triple therapy)/open-label (dual therapy) study conducted in the United States and Europe in treatment-naïve H. pylori-positive adult patients [see Clinical Studies (14.4)].

Adverse Reactions Leading to Discontinuation

Treatment discontinuation due to an adverse reaction occurred in 2.3% (8/346) of the patients treated with VOQUEZNA, amoxicillin, and clarithromycin; 0.9% (3/348) of the patients treated with VOQUEZNA and amoxicillin; and 1.2% (4/345) of the patients treated with lansoprazole, amoxicillin, and clarithromycin. The most common adverse reactions leading to discontinuation of VOQUEZNA, amoxicillin, and clarithromycin were diarrhea (0.6%) and hypertension (0.6%), and the most common adverse reaction leading to discontinuation of VOQUEZNA and amoxicillin was rash (0.6%).

Most Common Adverse Reactions

Adverse reactions reported in at least 2% of patients in any treatment arm are described in Table 8.

Table 8: Adverse Reactions [Reported in at least 2% of patients in any treatment arm.] in Adult Patients with H. pylori Infection [These trials were not designed to support comparative claims for VOQUEZNA-containing treatment arms for the adverse reactions reported in this table.]
Adverse Reactions | VOQUEZNA and Amoxicillin | VOQUEZNA, Amoxicillin, and Clarithromycin | Lansoprazole, Amoxicillin, and Clarithromycin
 | N=348 % | N=346 % | N=345 %
Diarrhea | 5 | 4 | 10
Dysgeusia [Represents a grouped term and includes related terms.] | 1 | 5 | 6
Vulvovaginal candidiasis | 2 | 3 | 1
Abdominal pain | 3 | 2 | 3
Headache | 1 | 3 | 1
Hypertension | 1 | 2 | 1
Nasopharyngitis | 2 | <1 | 1

Less Common Adverse Reactions

Other adverse reactions reported in less than 2% of patients treated with VOQUEZNA, amoxicillin, and clarithromycin or VOQUEZNA and amoxicillin are listed below by body system:

Blood and lymphatic system disorders: anemia, leukocytosis, leukopenia, neutropenia

Cardiac disorders: QT prolongation, tachycardia

Eye disorders: orbital edema

Gastrointestinal disorders: abdominal distension, constipation, dry mouth, duodenal polyp, duodenal ulcer, dyspepsia, flatulence, gastric ulcer, gastroesophageal reflux disease, hematochezia, large intestine polyp, rectal polyp, nausea, stomatitis, tongue discomfort, vomiting

General disorders and administration site conditions: fatigue, pyrexia

Immune system disorders: drug hypersensitivity

Infections and infestations: anal fungal infection, gastrointestinal viral infection, oral fungal infection, pneumonia, tongue fungal infection, upper respiratory tract infection, urinary tract infection, viral infection

Investigations: increased liver function test

Metabolism and nutrition disorders: decreased appetite

Musculoskeletal system: bone fracture

Nervous system disorders: ageusia, dizziness, tension headache

Psychiatric disorders: anxiety, depression, insomnia

Renal and urinary disorders: renal hypertrophy, tubulointerstitial nephritis

Reproductive system and breast disorders: vaginal discharge

Respiratory, thoracic and mediastinal disorders: cough, nasal polyps, oropharyngeal pain

Skin and subcutaneous tissue disorders: dermatitis, dry skin, rash

For more information on adverse reactions and laboratory changes with amoxicillin or clarithromycin, refer to the Adverse Reactions section of the corresponding prescribing information.

6.2 Postmarketing Experience

The following additional adverse reactions have been identified during post-approval use of vonoprazan outside of the United States. Because these reactions are reported voluntarily from a population of uncertain size, it is not always possible to reliably estimate their frequency or establish a causal relationship to drug exposure.

Blood and lymphatic system disorders: thrombocytopenia

Immune system disorders: anaphylactic shock [see Contraindications (4)]

Infections and infestations: C. difficile (with concomitant antibacterials)

Investigation: hypomagnesemia, hypokalemia, hypocalcemia, vitamin B12 deficiency

Hepatobiliary disorders: hepatic injury, hepatic failure, jaundice

Skin and subcutaneous tissue disorders: drug eruption, erythema multiforme, Stevens-Johnson syndrome, toxic epidermal necrolysis

7 DRUG INTERACTIONS

Table 9 and Table 10 include drugs with clinically important drug interactions and interaction with diagnostics when administered concomitantly with VOQUEZNA and instructions for preventing or managing them.

These recommendations are based on either drug interaction trials or predicted interactions due to the expected magnitude of interaction and potential for serious adverse reactions or loss of efficacy [see Clinical Pharmacology (12.3)].

Consult the labeling of concomitantly used drugs to obtain further information about interactions with vonoprazan.

Table 9: Drug Interactions Affecting Drugs Co-Administered with VOQUEZNA and Interactions with Diagnostics
Drugs Dependent on Gastric pH for Absorption
Antiretrovirals
Clinical Effect | Vonoprazan reduces intragastric acidity [see Clinical Pharmacology (12.2)], which may alter the absorption of antiretroviral drugs, leading to changes in the safety and/or effectiveness.
Prevention or Management | Rilpivirine-containing products | Concomitant use with VOQUEZNA is contraindicated.
Prevention or Management | Atazanavir | Avoid concomitant use with VOQUEZNA.
Prevention or Management | Nelfinavir | Avoid concomitant use with VOQUEZNA.
Prevention or Management | Other antiretrovirals | See the prescribing information of other antiretroviral drugs dependent on gastric pH for absorption prior to concomitant use with VOQUEZNA.
Other Drugs (e.g., iron salts, erlotinib, dasatinib, nilotinib, mycophenolate mofetil, ketoconazole/itraconazole)
Clinical Effect | Vonoprazan reduces intragastric acidity [see Clinical Pharmacology (12.2)], which may decrease the absorption of drugs reducing their effectiveness.
Prevention or Management | See the prescribing information for other drugs dependent on gastric pH for absorption.
Combination Therapy with Clarithromycin and/or Amoxicillin
Clinical Effect | Concomitant administration of clarithromycin with other drugs can lead to serious adverse reactions, including potentially fatal arrhythmias, and is contraindicated. Amoxicillin also has drug interactions.
Prevention or Management | See Contraindications and Warnings and Precautions in the prescribing information for clarithromycin. See Drug Interactions in the prescribing information for amoxicillin.
Certain CYP3A Substrates Where Minimal Concentration Changes May Lead to Serious Toxicities
Clinical Effect | Vonoprazan is a weak CYP3A inhibitor [see Clinical Pharmacology (12.3)]. Vonoprazan may increase exposure of CYP3A4 substrates, which may increase the risk of adverse reactions related to these substrates.
Prevention or Management | Frequently monitor concentrations and/or adverse reactions related to the substrate drugs when used with VOQUEZNA. Dosage reduction of substrate drugs may be needed. See prescribing information for the relevant substrate drugs.
CYP2C19 Substrates (e.g., clopidogrel, citalopram, cilostazol)
Clinical Effect | Vonoprazan is a CYP2C19 inhibitor [see Clinical Pharmacology (12.3)]. Vonoprazan may reduce plasma concentrations of the active metabolite of clopidogrel and may cause reduction in platelet inhibition. Vonoprazan may increase exposure of CYP2C19 substrate drugs (e.g., citalopram, cilostazol).
Prevention or Management | Clopidogrel | Carefully monitor the efficacy of clopidogrel and consider alternative anti-platelet therapy.
Prevention or Management | Citalopram and Cilostazol | Carefully monitor patients for adverse reactions associated with citalopram and cilostazol. See the prescribing information for dosage adjustments.
Chromogranin Test for Neuroendocrine Tumors
Clinical Effect | Vonoprazan reduces intragastric acidity [see Clinical Pharmacology (12.2)], which increases CgA levels and may cause false positive results in diagnostic investigations for neuroendocrine tumors.
Prevention or Management | Assess CgA levels at least 4 weeks after stopping VOQUEZNA treatment and repeat the test if initial CgA levels are high. If serial tests are performed (e.g., for monitoring), use the same commercial laboratory for testing, as reference ranges between tests may vary.
Interaction with Secretin Stimulation Test
Clinical Effect | Hyper-response in gastrin secretion in response to secretin stimulation test, falsely suggesting gastrinoma.
Prevention or Management | Temporarily stop VOQUEZNA at least 4 weeks before assessing to allow gastrin levels to return to normal [see Clinical Pharmacology (12.2)].

Table 10: Drug Interactions Affecting VOQUEZNA When Co-Administered with Other Drugs
Strong or Moderate CYP3A4 Inducers
Clinical Effect | Vonoprazan is a CYP3A substrate. Strong or moderate CYP3A inducers decrease vonoprazan exposure [see Clinical Pharmacology (12.3)], which may reduce the effectiveness of VOQUEZNA.
Prevention or Management | Avoid concomitant use with VOQUEZNA.

8 USE IN SPECIFIC POPULATIONS

8.1 Pregnancy

Pregnancy Exposure Registry

There is a pregnancy exposure registry that monitors pregnancy outcomes in women exposed to VOQUEZNA during pregnancy. Healthcare providers are encouraged to register patients by calling 1-866-609-1612 or visiting https://voqueznapregnancyregistry.com/.

Risk Summary

There are no adequate and well-controlled studies of vonoprazan in pregnant women. Available data from pharmacovigilance reports with vonoprazan-containing products used in pregnant women are not sufficient to evaluate for a drug-associated risk for major birth defects, miscarriage, or other adverse maternal or fetal outcomes.

In pregnant rats, no adverse effects were noted after oral administration of vonoprazan during organogenesis at approximately 27-times the maximum recommended human dose (MRHD), based on AUC exposure comparisons.

In a pre- and postnatal development (PPND) study, pups from dams orally administered vonoprazan during organogenesis and through lactation exhibited liver discoloration, which, in follow-up mechanistic animal studies, was associated with necrosis, fibrosis, and hemorrhage at a dose approximately 22-times the MRHD, based on AUC comparisons that were likely attributable to exposure during lactation [see Use in Specific Populations (8.2)]. These effects were not observed at the next lower dose in this study, which was approximately equal to the MRHD, based on AUC comparison; however, they were seen at clinically relevant exposures in dose range-finding studies in rats (see Data).

The background risks of major birth defects and miscarriage for the indicated population are unknown. All pregnancies have a background risk of birth defects, loss, or other adverse outcomes. In the United States general population, the estimated background risk of major birth defects and miscarriage in clinically recognized pregnancies is 2% to 4% and 15% to 20%, respectively.

Data

Animal Data

Pregnant rats were orally administered vonoprazan at doses of 30, 100, or 300 mg/kg/day (7-, 27-, 130-times the MRHD based on AUC comparison at the same doses from unmated female rats from separate studies) during the period of organogenesis from gestation day (GD) 6 to 17. During maternal dosing, one high-dose female died and decreased body weight and food consumption occurred at the middle and highest doses. No embryo-fetal lethality was observed but decreased fetal body weight was observed in the highest dose group. Fetal abnormalities were limited to the 300 mg/kg/day and included ventricular septal defect and mal-positioned subclavian artery in fetuses in a majority (15/19) of litters, as well as tail abnormalities and small anal opening. No adverse embryo-fetal effects were observed at the 100 mg/kg/day.

Pregnant rabbits were orally administered vonoprazan at doses of 3, 10, or 30 mg/kg/day (0.04-, 1.5-, 10-times the MRHD based on AUC comparison) during the period of organogenesis from GD 6 to 18. Two animals aborted at the highest dose and decreased body weight and food consumption occurred at the mid and high doses. No embryo-fetal mortality or toxicity occurred. There were no external, visceral, or skeletal abnormalities.

In a PPND study, pregnant female rats were orally administered vonoprazan at doses of 1, 3, 10, or 100 mg/kg/day (0.01-, 0.18-, 1.1-, 22-times the MRHD based on AUC comparison) from GD 6 to lactation day (LD) 21. Decreased body weight gain and food consumption were present in dams at the highest dose during lactation. Decreased body weight gain compared to controls was observed in the offspring from dams in the high dose group. Liver discoloration occurred in offspring from the high dose group at LD 4 but was not present in animals examined after weaning. Similarly, in dose range-finding studies in rats and follow-up mechanistic animal studies, the liver discoloration was observed and characterized as necrosis, fibrosis, and hemorrhage at equal to or greater than clinically relevant exposures based on AUC comparisons. The mechanistic studies further demonstrated the effect was likely attributable to vonoprazan exposure during lactation [see Use in Specific Populations (8.2)]. The clinical relevance of the liver findings is uncertain.

Exposure margins from vonoprazan between the animal and clinical studies for vonoprazan, amoxicillin, and clarithromycin used in combination may be lower due to increased vonoprazan exposure from concomitant use with clarithromycin in patients [see Clinical Pharmacology (12.3)].

8.2 Lactation

Risk Summary

Data from a clinical lactation study indicate that vonoprazan is present in human breast milk in amounts less than 0.03% of the administered maternal dose. Assuming an infant body weight of 6 kg and an exclusively breastfed infant, the estimated mean daily infant dose was less than 0.3% of the maternal weight-adjusted dose (see Data). There are no data on the effects of vonoprazan on the breastfed child or the effects on milk production. In animal studies, liver injury occurred in offspring from pregnant and lactating rats administered oral vonoprazan at AUC exposures approximately equal to and greater than the MRHD (see Data).

The developmental and health benefits of breastfeeding should be considered along with the mother’s clinical need for VOQUEZNA and any potential adverse effects on the breastfed child from VOQUEZNA or from the underlying maternal condition.

Data

Human Data

Concentrations of vonoprazan were measured in breast milk from 15 healthy lactating women following administration of vonoprazan 20 mg once daily (N=5) or twice daily (N=10) for 4 days (not an approved duration for VOQUEZNA).

Following administration of a 20 mg vonoprazan once daily regimen, the mean average concentration (Cavg) of vonoprazan in breast milk at steady state was 7.55 ng/mL. The estimated mean total amount of vonoprazan present in breast milk over 24 hours was 0.0024 mg. Assuming an infant body weight of 6 kg and an exclusively breastfed infant, the estimated mean daily infant dose was 0.0004 mg/kg/day, representing 0.13% of the maternal weight-adjusted dose.

Following administration of a 20 mg vonoprazan twice daily dosage regimen, the mean average concentration (Cavg) of vonoprazan in breast milk at steady state was 13.3 ng/mL. The estimated mean total amount of vonoprazan present in breast milk over 24 hours was 0.009 mg. Assuming an infant body weight of 6 kg and an exclusively breastfed infant, the estimated mean daily infant dose was 0.0015 mg/kg/day, representing 0.27% of the maternal weight-adjusted dose.

Animal Data
In a PPND study in rats, in which the dams were administered oral vonoprazan during gestation and through lactation at up to 22-times the MRHD (based on a comparison of AUC), liver discoloration occurred in offspring from the high dose group [see Use in Specific Populations (8.1)].

Liver discoloration associated with necrosis, fibrosis, and hemorrhage in the offspring of dosed rats was also seen in dose-range finding studies and limited, non-standard, follow-up, mechanistic studies, including offspring in lactation only studies. These effects were reported in pups on LD 4 at doses from 3 to 100 mg/kg/day (approximately 0.2-to 22-fold the MRHD based on an AUC values extrapolated from the PPND study) and on LD 14 at doses from 10 to 100 mg/kg/day (approximately 1-to 22-fold the MRHD based on an extrapolated AUC comparisons). In mechanistic studies, liver effects were observed in offspring treated only during lactation but not in offspring from animals only treated during gestation. In some of these studies, this finding was associated with increased offspring stomach weights that was reversed along with liver discoloration by concomitant treatment with a gastrointestinal prokinetic agent.

8.4 Pediatric Use

The safety and effectiveness of VOQUEZNA have not been established in pediatric patients.

8.5 Geriatric Use

There were 200 patients aged 65 years and older in the clinical trial for healing and maintenance of healed erosive esophagitis [see Clinical Studies (14.1)]. Of the total number of vonoprazan-treated patients, there were 93 (18%) patients aged 65 years of age and older and 10 (2%) patients aged 75 years of age and older.

There were 139 patients aged 65 years and older in the clinical trial for the relief of heartburn associated with non-erosive gastroesophageal reflux disease [see Clinical Studies (14.3)]. Of the total number of vonoprazan-treated patients, there were 93 (18%) patients aged 65 years of age and older and 14 (3%) patients aged 75 years of age and older.

There were 218 patients aged 65 years and older in the clinical trial for the treatment of H. pylori infection [see Clinical Studies (14.4)]. Of the total number of vonoprazan-treated patients, there were 153 (22%) patients aged 65 years of age and older and 18 (3%) patients aged 75 years of age and older.

No overall differences in safety or effectiveness were observed between these patients and younger adult patients, and other reported clinical experience has not identified differences in responses between the geriatric and younger adult patients, but greater sensitivity of some older individuals cannot be ruled out.

No clinically meaningful differences in the pharmacokinetics of vonoprazan are predicted in patients 65 years of age and older compared to younger adult patients [see Clinical Pharmacology (12.3)].

8.6 Renal Impairment

Healing of Erosive Esophagitis

No dosage adjustment of VOQUEZNA for the healing of erosive esophagitis is recommended in patients with mild to moderate renal impairment (eGFR 30 to 89 mL/min). Dosage reduction is recommended in patients with severe renal impairment (eGFR < 30 mL/min) [see Dosage and Administration (2.2) and Clinical Pharmacology (12.3)].

Maintenance of Healed Erosive Esophagitis or Relief of Heartburn Associated with Non-Erosive Gastroesophageal Reflux Disease

No dosage adjustment of VOQUEZNA for the maintenance of healed erosive esophagitis or the relief of heartburn associated with non-erosive gastroesophageal reflux disease is recommended in patients with any degree of renal impairment.

Treatment of H. pylori Infection

Use of VOQUEZNA is not recommended for the treatment of H. pylori infection in patients with severe renal impairment (eGFR < 30 mL/min) [see Dosage and Administration (2.2) and Clinical Pharmacology (12.3)].

8.7 Hepatic Impairment

Healing of Erosive Esophagitis

No dosage adjustment of VOQUEZNA for the healing of erosive esophagitis is recommended in patients with mild hepatic impairment (Child-Pugh A). Dosage reduction is recommended in patients with moderate to severe hepatic impairment (Child-Pugh Class B and C) [see Dosage and Administration (2.3) and Clinical Pharmacology (12.3)].

Maintenance of Healed Erosive Esophagitis or Relief of Heartburn Associated with Non-Erosive Gastroesophageal Reflux Disease

No dosage adjustment of VOQUEZNA for the maintenance of healed erosive esophagitis or the relief of heartburn associated with non-erosive gastroesophageal reflux disease is recommended in patients with any degree of hepatic impairment.

Treatment of H. pylori Infection

Use of VOQUEZNA is not recommended for the treatment of H. pylori infection in patients with moderate to severe hepatic impairment (Child-Pugh Class B and C) [see Dosage and Administration (2.3) and Clinical Pharmacology (12.3)].

11 DESCRIPTION

Vonoprazan (as the fumarate), is a potassium-competitive acid blocker. Chemically, it is 1H-pyrrole-3-methanamine, 5-(2-fluorophenyl)-N-methyl-1-(3-pyridinylsulfonyl)-, (2E)-2-butenedioate (1:1). Its empirical formula is C17H16FN3O2S•C4H4O4 with a molecular weight of 461.5. Vonoprazan fumarate has the following structure:

Vonoprazan fumarate is white to nearly white crystals or crystalline powder, which melts at 194.8°C. Vonoprazan fumarate is soluble in dimethyl sulfoxide; sparingly soluble in N,N–dimethylacetamide, slightly soluble in N,N-dimethylformamide, methanol, and water; very slightly soluble in ethanol (99.5%); and practically insoluble in 2-propanol, acetone, 1-octanol, and acetonitrile.

VOQUEZNA (vonoprazan) tablets are available in two dosage strengths for oral administration: 10 mg of vonoprazan (equivalent to 13.36 mg of vonoprazan fumarate) and 20 mg of vonoprazan (equivalent to 26.72 mg of vonoprazan fumarate). Each film-coated tablet contains the following inactive ingredients: ascorbic acid, croscarmellose sodium, ferric oxide red (only in 20 mg tablets), ferric oxide yellow (only in 10 mg tablets), fumaric acid, hydroxypropyl cellulose, hypromellose, magnesium stearate, mannitol, microcrystalline cellulose, polyethylene glycol 8000, and titanium dioxide.

12 CLINICAL PHARMACOLOGY

12.1 Mechanism of Action

Vonoprazan suppresses basal and stimulated gastric acid secretion at the secretory surface of the gastric parietal cell through inhibition of the H^+, K^+-ATPase enzyme system in a potassium-competitive manner. Because this enzyme is regarded as the acid (proton) pump within the parietal cell, vonoprazan has been characterized as a type of gastric proton-pump inhibitor, in that it blocks the final step of acid production. Vonoprazan does not require activation by acid. Vonoprazan may selectively concentrate in the parietal cells in both the resting and stimulated states. Vonoprazan binds to the active pumps in a noncovalent and reversible manner.

12.2 Pharmacodynamics

Antisecretory Activity

Following a single 10 mg or 20 mg dose of vonoprazan, the onset of the antisecretory effect, as measured by intragastric pH, occurs within 2 to 3 hours. The elevated intragastric pH levels compared to placebo increase with dose and are maintained for over 24 hours after dosing. The inhibitory effect of vonoprazan on acid secretion increases with repeated daily dosing and steady state is achieved by Day 4. The antisecretory effect of vonoprazan decreases following drug discontinuation although intragastric pH remained elevated compared to placebo for 24 to 48 hours following the dose on Day 7.

The effects of vonoprazan 10 mg or 20 mg once daily for 7 days on 24-hour intragastric pH in healthy subjects are shown in Table 11.

Table 11: Effect of VOQUEZNA 10 mg or 20 mg Once Daily on 24-Hour Intragastric pH at Baseline and on Days 1 and 7 in Healthy Subjects
Parameter | VOQUEZNA 10 mg Once Daily (N=9) |  |  | VOQUEZNA 20 mg Once Daily (N=9)
Parameter | Baseline | Day 1 | Day 7 | Baseline | Day 1 | Day 7
Mean Intragastric pH | 2.0 | 3.7 | 4.6 | 1.9 | 4.5 | 5.9
% Time Intragastric pH>4 (hours) | 6.8 (2 h) | 43.1 (10 h) | 60.2 (14 h) | 7.4 (2 h) | 62.7 (15 h) | 85.2 (20 h)
% Time Intragastric pH>6 (hours) | 1.3 (<1 h) | 20.7 (5 h) | 34.3 (8 h) | 0.9 (<1 h) | 29.0 (7 h) | 57.8 (14 h)

Cardiac Electrophysiology

At a single dose of 120 mg (6-times the maximum recommended dose), vonoprazan does not prolong the QT interval to any clinically relevant extent.

Serum Gastrin Effects

The effect of vonoprazan on serum gastrin concentrations was evaluated in clinical trials for the healing of erosive esophagitis, maintenance of healed erosive esophagitis, and relief of heartburn associated with non-erosive gastroesophageal reflux disease [see Clinical Studies (14)]. In patients with erosive esophagitis treated with VOQUEZNA 20 mg once daily, the mean fasting gastrin levels at Week 2 increased from baseline and levels were similar at Week 2 and Week 8. During maintenance treatment for healed erosive esophagitis with VOQUEZNA 10 mg once daily, the mean gastrin levels remained elevated and returned to normal within 4 weeks of discontinuation of treatment.

In patients with non-erosive gastroesophageal reflux disease treated with VOQUEZNA 10 mg once daily, the mean fasting gastrin levels increased from baseline, remained elevated during treatment, and returned to normal within 4 weeks of discontinuation of treatment.

Increased gastrin causes enterochromaffin-like cell hyperplasia and increased serum CgA levels. The increased CgA levels may cause false positive results in diagnostic investigations for neuroendocrine tumors [see Warnings and Precautions (5.8) and Drug Interactions (7)].

Enterochromaffin-Like Cell (ECL) Effects

Human gastric biopsy specimens were obtained from 135 patients treated with vonoprazan 10 mg or 20 mg once daily for up to 260 weeks. An increase in the incidence of hyperplasia of the parietal cells and G-cells was observed, which is consistent with the pharmacological action of a potassium-competitive acid blocker. No neoplastic changes were observed [see Nonclinical Toxicology (13.1), (13.2)].

12.3 Pharmacokinetics

Steady state pharmacokinetic (PK) parameters for vonoprazan 10 mg or 20 mg following once daily administration and vonoprazan 20 mg following twice daily administration from data collected across multiple studies are summarized in Table 12.

Table 12: Mean (%CV) Steady State Pharmacokinetic Parameters For Vonoprazan Following Once or Twice Daily Dosing
PK Parameter | Vonoprazan 10 mg | Vonoprazan 20 mg
PK Parameter | Once Daily (N=30) | Once Daily (N=68) | Twice Daily (N=32)
Tmax(h) median (min, max) | 1.5 (0.75, 3.0) | 2.0 (0.75, 5.0) | 3.0 (1.0-6.0)
Cmax (ng/mL) | 11.7 (27.5) | 26.1 (35.2) | 37.8 (36.1)
AUC (hr*ng/mL) | 92.9 (33.1) [AUC0-24h] | 230.9 (41.3) | 272.5 (30.5) [AUC0-12h]
t1/2z (h) | 7.7 (27.1) | 7.9 (22.6) | 6.8 (22.7)
CL/F (L/h) | 120.2 (35.2) | 100.2 (38.3) | 81.3 (35.7)
Vz/F (L) | 1270.7 (26.6) | 1114.0 (39.6) | 782.7 (34.4)

Cmax = Maximum plasma concentration; AUC0-24h = Area under the plasma concentration-time curve from time 0 to end of the 24-hour dosing interval; AUC0-12h = Area under the plasma concentration-time curve from time 0 to the end of the 12-hour dosing interval; Tmax = Time to reach Cmax, t1/2 = Elimination half-life, CL/F = Apparent oral clearance, Vz/F = Apparent oral volume of distribution

Absorption

Vonoprazan exhibits time-independent pharmacokinetics and steady state concentrations are achieved by Day 3 to 4. After multiple doses of vonoprazan ranging from 10 to 40 mg (twice the maximum recommended dose) once daily for 7 days in healthy subjects, Cmax and area under the plasma concentration-time curve (AUC) values for vonoprazan increased in an approximately dose-proportional manner.

There is little accumulation in plasma after once daily multiple doses, with an accumulation index ratio of less than 1.2 based on AUC for doses ranging from 10 to 40 mg (twice the maximum recommended dose).

Steady state plasma exposure of vonoprazan following 20 mg twice daily dosing (AUC0-12h = 273 hr*ng/mL, N=10) was approximately 1.8-fold higher compared to the mean estimate from the same subjects on Day 1 (AUC0-12h = 155 hr*ng/mL, N=10).

Effect of Food

In a food effect study in healthy subjects (N=24) who received vonoprazan 20 mg, a high-fat meal resulted in a 5% increase in Cmax, a 15% increase in AUC, and a delay in median Tmax of 2 hours. These changes are not considered to be clinically significant [see Dosage and Administration (2.4)].

Distribution

Plasma protein binding of vonoprazan ranged from 85 to 88% in healthy subjects and was independent of concentration from 0.1 to 10 mcg/mL.

Elimination

Metabolism

Vonoprazan is metabolized to inactive metabolites via multiple pathways by a combination of cytochrome P450 (CYP) isoforms (predominantly CYP3A4/5, CYP2C19, CYP2D6, and CYP2B6) along with sulfo- and glucuronosyl-transferases. CYP2C19 and CYP2D6 polymorphisms have been evaluated in clinical studies and there were no clinically meaningful differences in the pharmacokinetics of vonoprazan based on either CYP2C19 or CYP2D6 metabolizer status.

Excretion

Following oral administration of radiolabeled vonoprazan, approximately 67% of the radiolabeled dose (8% as unchanged vonoprazan) was recovered in urine and 31% (1.4% as unchanged vonoprazan) was recovered in feces.

Specific Populations

Geriatric Patients

No clinically meaningful differences in the pharmacokinetics of vonoprazan are predicted in patients 65 years of age and older compared to younger adult patients.

Sex, Race, or Ethnicity

There were no clinically significant differences in the pharmacokinetics of vonoprazan based on sex or race/ethnicity.

Patients with Renal impairment

The pharmacokinetics of vonoprazan administered as a single 20 mg dose in patients with mild [eGFR 60 to <90 mL/min/1.73 m^2 (N=8)], moderate [eGFR 30 to <60 mL/min/1.73 m^2 (N=8)], or severe [eGFR 15 to <30 mL/min/1.73 m^2 (N=8)] renal impairment were compared to those with normal renal function [eGFR ≥90 mL/min/1.73 m^2 (N=13)]. Compared to subjects with normal renal function, systemic exposure (AUC0-inf) was 1.7-, 1.3-, and 2.4-times greater in patients with mild, moderate, and severe renal impairment, respectively. In subjects requiring dialysis (N=8), AUC0-inf estimates were 1.3-fold greater compared to estimates from subjects with normal renal function [see Dosage and Administration (2.2)]. Protein binding of vonoprazan is not affected by impaired renal function. In patients requiring dialysis, vonoprazan was present in the dialysate and represented 0.94% of the dose administered.

Patients with Hepatic Impairment

The pharmacokinetics of vonoprazan administered as a single 20 mg dose in patients with mild [Child-Pugh Class A (N=8)], moderate [Child-Pugh Class B (N=8)], or severe [Child-Pugh Class C (N=6)] hepatic impairment were compared to those with normal hepatic function (N=12). Compared to subjects with normal hepatic function, systemic exposure (AUC0-inf) of vonoprazan was 1.2-, 2.4-, and 2.6-times greater in patients with mild, moderate, and severe hepatic impairment, respectively [see Dosage and Administration (2.3)]. Protein binding of vonoprazan is not affected by impaired hepatic function.

Drug Interaction Studies

In Vitro Studies

Cytochrome P450 (CYP450) Enzymes

In vitro studies have shown that vonoprazan directly and time-dependently inhibits CYP2B6, CYP2C19, and CYP3A4/5.

Transporter Systems

Vonoprazan inhibits multidrug and toxin extrusion protein 1 (MATE1) and organic cation transporter 1 (OCT1), but only at concentrations higher than clinically relevant.

Clinical Studies

Combination Therapy with Vonoprazan, Amoxicillin, and Clarithromycin

When vonoprazan 20 mg, amoxicillin 750 mg, and clarithromycin 400 mg were co-administered twice daily for 7 days (N=11), there was no effect on pharmacokinetics of amoxicillin compared to amoxicillin alone. However, vonoprazan Cmax and AUC0-12h increased by 87% and 85%, respectively, and clarithromycin Cmax and AUC0-12h increased by 64% and 45%, respectively, compared to administration of each component alone.

Effect of Vonoprazan on CYP3A4 Substrates

When a single oral dose of midazolam 2 mg was administered following vonoprazan 20 mg twice daily for 7 days (N=20), midazolam AUC0-inf increased 93% compared to administration of midazolam alone.

Effect of CYP3A Inhibitors on Vonoprazan

When a single dose of 40 mg vonoprazan (twice the maximum recommended dose) was administered with clarithromycin 500 mg twice daily for 7 days (N=16), vonoprazan AUC0-inf increased 58% compared to administration of vonoprazan alone.

Coadministration of Vonoprazan with Non-Steroidal Anti-Inflammatory Drugs (NSAIDs) or Low-Dose Aspirin

When a single dose of 40 mg vonoprazan (twice the maximum recommended dose) was co-administered with diclofenac 25 mg, meloxicam 10 mg, or aspirin 100 mg, there were no clinically meaningful changes in exposure of vonoprazan, diclofenac, meloxicam, or aspirin compared to administration of each drug alone.

Model-Informed Approaches

Effect of CYP3A Inducers on Vonoprazan

Vonoprazan exposures are predicted to be 80% lower when co-administered with a strong CYP3A4 inducer such as rifampicin and 50% lower when co-administered with a moderate CYP3A4 inducer such as efavirenz.

12.4 Microbiology

Antimicrobial Activity

Culture and sensitivity testing of bacteria are not routinely performed to establish the diagnosis of H. pylori infection [see Clinical Studies (14.4)]. The following in vitro data are available, but their clinical significance is unknown. Clarithromycin and amoxicillin are active in vitro against most isolates of H. pylori.

Susceptibility Testing

For specific information regarding susceptibility test interpretive criteria and associated test methods and quality control standards recognized by FDA for this drug, please see: https://www.fda.gov/STIC.

13 NONCLINICAL TOXICOLOGY

13.1 Carcinogenesis, Mutagenesis, Impairment of Fertility

Carcinogenicity

In a 24-month carcinogenicity study in mice, vonoprazan at daily oral doses of 6, 20, 60, and 200 mg/kg/day (approximately 0.4-, 4-, 19-, and 93-times the MRHD based on AUC) produced hyperplasia of neuroendocrine cells, gastropathy, and benign and/or malignant neuroendocrine cell tumors (carcinoids) in the stomach at all doses in males and at 60 mg/kg/day and greater in females. In the liver, increased incidences of hepatocellular adenoma and carcinomas were observed at doses of 20 mg/kg/day and greater in males and 60 mg/kg/day and greater in females.

In a 24-month carcinogenicity study in Sprague-Dawley rats, vonoprazan at daily oral doses of 5, 15, 50, and 150 mg/kg/day (approximately 0.6-, 4-, 19-, and 65-times the MRHD based on AUC) produced benign and/or malignant neuroendocrine cell tumors in the stomach in both male and female rats at doses of 5 mg/kg/day or more. Increased incidence of hepatocellular adenoma and carcinomas and hepatocholangiocellular adenomas and carcinomas were observed at doses of 50 and 150 mg/kg/day.

In both mice and rats, neuroendocrine tumors in the stomach occurred in association with neuroendocrine hyperplasia, and gastropathy in the stomach and increased plasma gastrin concentrations that are consistent with inhibition of gastric acid secretion. Carcinoid tumors have also been observed in rats subjected to fundectomy or long-term treatment with PPIs or high doses of H2-receptor antagonists.

Mutagenesis

Vonoprazan was negative for mutagenicity in the in vitro Ames test, in an in vitro clastogenicity assay in Chinese Hamster cells and in vivo in a rat bone marrow micronucleus study.

Impairment of Fertility

Vonoprazan at oral doses up to 300 mg/kg/day in rats (approximately 133-times the MRHD based on AUC from a separate study in nonpregnant animals administered the same dose) was found to have no effect on fertility and reproductive performance. Elongation of the estrous cycle was observed in rats at doses equivalent to 133-times the MRHD, based on AUC.

13.2 Animal Toxicology and/or Pharmacology

During lifetime exposure of mice and rats dosed daily with up to 200 mg/kg/day and 150 mg/kg/day of vonoprazan, respectively, increases in gastrin levels and marked neuroendocrine hyperplasia and gastropathy were observed, followed by formation of carcinoid tumors [see Nonclinical Toxicology (13.1)]. This finding is considered to be a rodent-specific phenomenon.

14 CLINICAL STUDIES

14.1 Healing of Erosive Esophagitis and Relief of Heartburn

The effectiveness and safety of VOQUEZNA was evaluated in a randomized, active-controlled, double-blind, eight-week study conducted in the United States and Europe in 1024 adult patients with endoscopically confirmed erosive esophagitis (NCT04124926). Severity of the disease was classified based on the Los Angeles (LA) Classification Grading System (Grades A through D). Patients were randomized to one of the following treatment groups: VOQUEZNA 20 mg once daily or lansoprazole 30 mg once daily for 2 to 8 weeks. Patients who were positive for H. pylori infection or who had Barrett's esophagus and/or definite dysplastic changes in the esophagus at baseline were excluded from the study. Based on the LA Classification, 66% of patients had mild erosive esophagitis (Grades A or B) and 34% of patients had moderate to severe erosive esophagitis (Grades C or D) prior to randomization. Patients in the trial had a mean age of 51 years (range 18 to 84 years), 53% were female, 12% identified as Hispanic or Latino, 91% identified as White, 6% as Black or African American, and 3% identified as another racial group.

Healing of erosive esophagitis was assessed at Week 2 and Week 8 and resolution of heartburn symptoms was evaluated daily over the 8-week period. If endoscopic healing of erosive esophagitis was confirmed at Week 2, the patient entered the maintenance phase of the study. If endoscopic healing was not confirmed at Week 2, the patient continued to receive randomized treatment until Week 8. Only patients with confirmed endoscopic healing entered the maintenance phase. All endoscopies were centrally read and adjudicated.

Healing of All Grades of Erosive Esophagitis

The primary endpoint was endoscopically confirmed complete healing of all grades of erosive esophagitis at Week 2 or Week 8, as shown in Table 13.

Table 13: Rates of Healing of All LA Grades of Erosive Esophagitis in Adults at Week 2 or Week 8
Timepoint | Treatment Group |  | Treatment Difference (95% Confidence Interval)
Timepoint | VOQUEZNA 20 mg Once Daily | Lansoprazole 30 mg Once Daily | Treatment Difference (95% Confidence Interval)
 | N=514 % | N=510 %
Week 2 or 8 | 93 | 85 | 8 [Demonstrated non-inferiority to lansoprazole.] (4.5, 12.2)
Week 2 | 74 | 68

Healing of Erosive Esophagitis in Subgroups with LA Grade C or D Esophagitis

For the secondary endpoint of complete healing of erosive esophagitis at Week 2, superiority was demonstrated in the subgroup of patients with LA Grade C or D disease, 70% of 177 VOQUEZNA-treated patients and 53% of 174 lansoprazole-treated patients achieved healing (18% treatment difference; 95% CI 7.4, 27.4).

Complete healing of erosive esophagitis at either Week 2 or Week 8 in the subgroup of patients with LA Grade C or D disease was 92% in patients treated with VOQUEZNA and 72% in patients treated with lansoprazole. This endpoint was not statistically significant under the prespecified multiple testing procedure.

Relief of Heartburn in Patients with Erosive Esophagitis During the Healing Phase

The percentage of 24-hour heartburn-free days through Week 8 was evaluated as a secondary endpoint and results are shown in Table 14.

Table 14: Percentage of 24-Hour Heartburn-Free Days in Adults with Erosive Esophagitis Through Week 8
Parameter | Treatment Group |  | Treatment Difference (95% Confidence Interval)
Parameter | VOQUEZNA 20 mg Once Daily N=514 % | Lansoprazole 30 mg Once Daily N=510 % | Treatment Difference (95% Confidence Interval)
Mean ± SD | 67 ± 35 | 64 ± 35 | 3 [Demonstrated non-inferiority to lansoprazole.] (-1.6, 7.0)
Median | 81 | 78

Other Healing of Erosive Esophagitis Studies

Two additional randomized, active-controlled, double-blind studies conducted outside of the United States, of similar design to the United States trial, also demonstrated non-inferiority of vonoprazan 20 mg once daily compared to lansoprazole 30 mg once daily for the primary endpoint of healing of all grades of erosive esophagitis by Week 8.

14.2 Maintenance of Healed Erosive Esophagitis and Relief of Heartburn

Patients who completed the healing phase of the erosive esophagitis study (NCT04124926) and showed endoscopically confirmed healed erosive esophagitis at Week 2 or Week 8 were re-randomized in the maintenance phase 1:1:1 to either VOQUEZNA 10 mg once daily, a higher dosage of VOQUEZNA, or lansoprazole 15 mg once daily. Maintenance of healing and resolution of heartburn symptoms were evaluated over 24 weeks. The higher VOQUEZNA dose group did not demonstrate additional treatment benefit compared to VOQUEZNA 10 mg once daily.

Maintenance of Healed Erosive Esophagitis

The primary endpoint was maintenance of healed erosive esophagitis (all grades) through Week 24. A secondary endpoint was maintenance of healed erosive esophagitis in the subgroup of patients with LA Grade C or D disease prior to randomization in the healing phase of the study.

The maintenance rates of healed erosive esophagitis are shown in Table 15.

Table 15: Maintenance Rates of Healed Erosive Esophagitis in Adults Through Week 24
Baseline Severity | Treatment Group |  | Treatment Difference (95% Confidence Interval)
Baseline Severity | VOQUEZNA 10 mg Once Daily | Lansoprazole 15 mg Once Daily | Treatment Difference (95% Confidence Interval)
All LA Grades: | N=293 | N=294
Week 24 | 79% | 72% | 7 [Demonstrated non-inferiority and superiority to lansoprazole.] (0.2, 14.1)
LA Grade C or D: | N=95 | N=96
Week 24 | 75% | 61% | 13 [Demonstrated superiority to lansoprazole.] (0.02, 26.1)

Relief of Heartburn During Maintenance of Healed Erosive Esophagitis

The percentage of 24-hour heartburn-free days through Week 24 was evaluated for non-inferiority as a secondary endpoint, as shown in Table 16.

Table 16: Percentage of 24-Hour Heartburn-Free Days in Adults with Healed Erosive Esophagitis Through Week 24
Parameter | Treatment Group |  | Treatment Difference (95% Confidence Interval)
Parameter | VOQUEZNA 10 mg Once Daily N=293 % | Lansoprazole 15 mg Once Daily N=294 % | Treatment Difference (95% Confidence Interval)
Mean ± SD | 81 ± 29 | 79 ± 27 | 2 [Demonstrated non-inferiority to lansoprazole.] (-2.3, 6.8)
Median | 95 | 89

Other Maintenance of Healed Erosive Esophagitis Studies

Two additional randomized, active-controlled, double-blind studies conducted outside of the United States, of similar design to the United States trial, also demonstrated non-inferiority of vonoprazan 10 mg once daily compared to lansoprazole 15 mg once daily for the primary endpoint of maintenance of healed erosive esophagitis (all grades) through Week 24.

14.3 Relief of Heartburn Associated with Non-Erosive Gastroesophageal Reflux Disease

The effectiveness and safety of VOQUEZNA was evaluated in a randomized, placebo-controlled, double-blind, four-week efficacy trial with a 20-week safety extension conducted in the United States in 772 adult patients with a diagnosis of symptomatic non-erosive gastroesophageal reflux disease (NCT05195528). Patients who identified heartburn as their primary symptom, had a history of heartburn for six months or longer, had heartburn on at least four of seven days immediately prior to randomization, were negative for H. pylori infection, and had no esophageal erosions as confirmed by endoscopy were enrolled. Patients were randomized 1:1:1 to one of the following treatment groups in the 4-week placebo-controlled phase: VOQUEZNA 10 mg once daily, a higher dosage of VOQUEZNA, or placebo once daily. The higher VOQUEZNA dose group did not demonstrate additional treatment benefit compared to VOQUEZNA 10 mg once daily through Week 4. Patients in the trial had a mean age of 51 years (range 18 to 83 years), 68% were female, 32% identified as Hispanic or Latino, 75% identified as White, 16% as Black or African American, 6% as Asian, and 3% identified as another racial group.

The primary endpoint was the percentage of 24-hour heartburn-free days, as assessed by daily diary over 4 weeks, as shown in Table 17.

Table 17: Percentage of 24-Hour Heartburn-Free Days in Patients with Non-Erosive Gastroesophageal Reflux Disease Through Week 4
 | Treatment Group
Parameter | VOQUEZNA 10 mg Once Daily N=257 % | Placebo Once Daily N=258 % | Treatment Difference (95% Confidence Interval)
LS Mean [Least squares mean of percentage of 24-hour heartburn-free days from analysis using a linear model, adjusted for baseline frequency and severity of heartburn.p<0.001] (SE) | 45 (2) | 28 (2) | 17 [p<0.001] (12, 22)
Median | 48 | 17
Mean = least squares mean
SE = standard error

The difference in the percentage of patients who were heartburn-free during the 24-hour period on Day 2 of treatment was similar to the difference in 24-hour heartburn-free days through Week 4 in patients treated with VOQUEZNA 10 mg once daily compared to patients treated with placebo.

14.4 Treatment of Helicobacter pylori Infection

The effectiveness and safety of VOQUEZNA, amoxicillin, and clarithromycin (triple therapy) and VOQUEZNA and amoxicillin (dual therapy) were evaluated in a randomized, controlled, double-blind (triple therapy)/open-label (dual therapy) study conducted in the United States and Europe in treatment-naïve H. pylori-positive adult patients with at least one clinical condition: dyspepsia lasting at least 2 weeks, functional dyspepsia, recent/new diagnosis of peptic ulcer, peptic ulcer not treated for H. pylori infection, or a stable dose of long-term NSAID treatment (NCT04167670). Patients were randomized 1:1:1 to one of the following regimens administered for 14 consecutive days:

- VOQUEZNA 20 mg twice daily, amoxicillin 1,000 mg twice daily, and clarithromycin 500 mg twice daily
- VOQUEZNA 20 mg twice daily and amoxicillin 1,000 mg three times daily
- lansoprazole 30 mg twice daily, amoxicillin 1,000 mg twice daily, and clarithromycin 500 mg twice daily

H. pylori infection at baseline was defined as positive by ^13C urea breath test (UBT) and follow-up upper endoscopy (culture or histology). H. pylori eradication was confirmed with a negative ^13C UBT test-of-cure at least 27 days post-therapy. Patients with negative test results were considered treatment successes. Patients who tested positive for H. pylori infection and patients with missing results from the test-of-cure visit were considered treatment failures.

A total of 346 patients received VOQUEZNA, amoxicillin, and clarithromycin, 348 patients received VOQUEZNA and amoxicillin, and 345 patients received lansoprazole, amoxicillin, and clarithromycin. These patients had a mean age of 51 years (range 20 to 87 years), 62% were female, 27% identified as Hispanic or Latino, 89% identified as White, 7% as Black or African American, 2% as Asian, and 2% identified as another racial group.

VOQUEZNA, amoxicillin, and clarithromycin and VOQUEZNA and amoxicillin were shown to be non-inferior to lansoprazole, amoxicillin, and clarithromycin in patients who did not have a clarithromycin- or amoxicillin-resistant strain of H. pylori at baseline. VOQUEZNA, amoxicillin, and clarithromycin and VOQUEZNA and amoxicillin were shown to be superior to lansoprazole, amoxicillin, and clarithromycin in patients who had a clarithromycin-resistant strain of H. pylori at baseline and in the overall population.

H. pylori eradication rates at least 27 days post-therapy are shown in Table 18.

Table 18: Eradication Rates of H. pylori in Adult Patients at Least 27 Days Post-Therapy - mITT
 | VOQUEZNA, Amoxicillin, and Clarithromycin | VOQUEZNA and Amoxicillin | Lansoprazole, Amoxicillin, and Clarithromycin (LAC)
 | % (n) | % (n) | % (n)
Patients with H. pylori infection who did not have a clarithromycin- or amoxicillin-resistant strain at baseline [Clarithromycin-resistant strains of H. pylori were considered those with an MIC ≥ 1 mcg/mL; amoxicillin-resistant strains were considered those with an MIC > 0.125 mcg/mL.] | 85 (222) | 79 (208) | 79 (201)
Treatment difference from LAC (95% CI) | 6 [p<0.0001 for test of non-inferiority versus LAC.] (-0.8, 12.6) | -0.3 [p<0.01 for test of non-inferiority versus LAC.] (-7.4, 6.8)
All randomized patients with H. pylori infection at baseline | 81 (273) | 77 (250) | 69 (226)
Treatment difference from LAC (95% CI) | 12 [p=0.0003 for test of superiority versus LAC.] (5.7, 18.8) | 9 [p=0.01 for test of superiority versus LAC.] (1.9, 15.4)
Patients with H. pylori infection who had a clarithromycin-resistant strain of H. pylori at baseline | 66 (48) | 70 (39) | 32 (23)
Treatment difference from LAC (95% CI) | 34 [p<0.0001 for test of superiority versus LAC.] (17.7, 48.1) | 38 (20.5, 52.6)
CI = confidence interval calculated via the Miettinen and Nurminen method.
Modified intent to treat (mITT) population: Patients were included in the mITT analysis if they had documented H. pylori infection at baseline.

16 HOW SUPPLIED/STORAGE AND HANDLING

VOQUEZNA (vonoprazan) tablets:

10 mg of vonoprazan: pale yellow, oval, film-coated tablets debossed V10 on one side and plain on the other side. Bottles of 30 (NDC 81520-100-30).

20 mg of vonoprazan: pale red, oval, film-coated tablets debossed V20 on one side and plain on the other side. Bottles of 30 (NDC 81520-200-30).

STORAGE AND HANDLING

Store between 20°C and 25°C (68°F and 77°F); excursions permitted between 15°C and 30°C (59°F and 86°F) [see USP Controlled Room Temperature].

17 PATIENT COUNSELING INFORMATION

Advise the patient to read the FDA-approved patient labeling (Patient Information).

Advise patients of the following:

Acute Tubulointerstitial Nephritis

To call their healthcare provider if they experience signs and/or symptoms associated with acute tubulointerstitial nephritis [see Warnings and Precautions (5.2)].

Clostridioides difficile-Associated Diarrhea

To immediately call their healthcare provider if they experience diarrhea that does not improve [see Warnings and Precautions (5.3)].

Bone Fracture

To report any fractures, especially of the hip, wrist, or spine, to their healthcare provider [see Warnings and Precautions (5.4)].

Severe Cutaneous Adverse Reactions

To discontinue VOQUEZNA and report to their healthcare provider at first appearance of a severe cutaneous adverse reaction or other sign of hypersensitivity [see Warnings and Precautions (5.5)].

Vitamin B12 (Cobalamin) Deficiency

To report any clinical symptoms that may be associated with Vitamin B12 deficiency to their healthcare provider, if they have been receiving VOQUEZNA long-term [see Warnings and Precautions (5.6)].

Hypomagnesemia and Mineral Metabolism

To report any clinical symptoms that may be associated with hypomagnesemia, hypocalcemia, and/or hypokalemia to their healthcare provider [see Warnings and Precautions (5.7)].

Drug Interactions

To report to their healthcare provider if they start treatment with rilpivirine-containing products [see Contraindications (4)].

Pregnancy

Advise patients that there is a pregnancy exposure registry that monitors pregnancy outcomes in women exposed to VOQUEZNA during pregnancy [see Use in Specific Populations (8.1)].

Important Administration Instructions

- VOQUEZNA can be taken with or without food [see Dosage and Administration (2) and Clinical Pharmacology (12.3)].
- Swallow VOQUEZNA tablets whole; do not chew or crush the tablet.
- Missed doses:
  - For the healing or maintenance of healed erosive esophagitis or for the relief of heartburn associated with non-erosive gastroesophageal reflux disease: If a dose is missed, administer VOQUEZNA as soon as possible within 12 hours after the missed dose. If more than 12 hours have passed, skip the missed dose and take your next dose at your regularly scheduled time [see Dosage and Administration (2)].
  - For the treatment of H. pylori infection: If a dose is missed, administer VOQUEZNA as soon as possible within 4 hours after the missed dose. If more than 4 hours have passed, skip the missed dose and administer your next dose at the regularly scheduled time. Continue the normal dosing schedule until the treatment is completed [see Dosage and Administration (2)].

VOQUEZNA is manufactured for and distributed by
Phathom Pharmaceuticals, Inc.
Buffalo Grove, IL 60089, U.S.A.

VOQUEZNA, the VOQUEZNA logo, and Phathom Pharmaceuticals are registered trademarks of Phathom Pharmaceuticals, Inc.

© 2025 Phathom Pharmaceuticals, Inc. All rights reserved.

VOQ222 V3

PATIENT INFORMATION
VOQUEZNA® (voe kwez nah)
(vonoprazan)
tablets, for oral use

What is VOQUEZNA?
VOQUEZNA is a prescription medicine called a potassium-competitive acid blocker. VOQUEZNA reduces the amount of acid in your stomach.
VOQUEZNA is used in adults:

- for 8 weeks to heal acid-related damage to the lining of the esophagus (called erosive esophagitis) and for relief of heartburn related to erosive esophagitis.
- for up to 6 months to maintain healing of erosive esophagitis and for relief of heartburn related to erosive esophagitis.
- for 4 weeks for relief of heartburn related to gastroesophageal reflux disease.
- for 14 days with the antibiotics amoxicillin and clarithromycin to treat an infection caused by bacteria called Helicobacter pylori (H. pylori).
- for 14 days with the antibiotic amoxicillin to treat an infection caused by bacteria called H. pylori.

It is not known if VOQUEZNA is safe and effective in children.

Do not take VOQUEZNA if you are:

- allergic to vonoprazan or any of the ingredients in VOQUEZNA. See the end of this Patient Information leaflet for a complete list of ingredients in VOQUEZNA. Allergic reaction symptoms may include trouble breathing, rash, itching, and swelling of your face, lips, tongue, or throat.
- taking a medicine that contains rilpivirine (EDURANT, JULUCA, ODEFSEY, COMPLERA) used to treat HIV-1 (Human Immunodeficiency Virus).

Before taking VOQUEZNA, tell your healthcare provider about all of your medical conditions, including if you:

- have low magnesium, calcium, or potassium in your blood or you are taking a medicine to increase urine (diuretic).
- have kidney problems.
- have liver problems.
- are pregnant, think you may be pregnant, or plan to become pregnant. It is not known if VOQUEZNA will harm your unborn baby.
  - Pregnancy Exposure Registry: There is a pregnancy registry for women who take VOQUEZNA during pregnancy. The purpose of this registry is to collect information about the health of you and your baby. If you are pregnant or become pregnant during treatment with VOQUEZNA, talk to your healthcare provider about how you can join this pregnancy registry or you can enroll in the registry by calling 1-866-609-1612 or visiting https://voqueznapregnancyregistry.com/.
- are breastfeeding or plan to breastfeed. You and your healthcare provider should decide if you will take VOQUEZNA while breastfeeding.

Tell your healthcare provider about all the medicines you take, including prescription and over-the-counter medicines, vitamins, and herbal supplements. Keep a list of them to show your healthcare provider and pharmacist when you get a new medicine. VOQUEZNA may affect how other medicines work, and other medicines may affect how VOQUEZNA works.

How should I take VOQUEZNA?

- Take VOQUEZNA exactly as your healthcare provider tells you to take it.
- Do not change your dose or stop taking VOQUEZNA without talking to your healthcare provider first.
- Take VOQUEZNA with or without food.
- Swallow VOQUEZNA tablets whole. Do not chew or crush the tablet.
- For the treatment of erosive esophagitis or the relief of heartburn related to gastroesophageal reflux disease:
  - If you miss a dose of VOQUEZNA, take it as soon as possible within 12 hours after the missed dose. If more than 12 hours have passed, skip the missed dose and take the next dose at the regularly scheduled time.
- For the treatment of H. pylori infection:
  - If you miss a dose of VOQUEZNA, take it as soon as possible within 4 hours after the missed dose. If more than 4 hours have passed, skip the missed dose and take the next dose at the regularly scheduled time. Continue your regular dosing schedule until the treatment is completed.

What are the possible side effects of VOQUEZNA?
VOQUEZNA may cause serious side effects, including:

- A type of kidney problem (acute tubulointerstitial nephritis). Some people who take VOQUEZNA may develop a kidney problem called acute tubulointerstitial nephritis. Call your healthcare provider right away if you have a decrease in the amount that you urinate or if you have blood in your urine.
- Diarrhea caused by an infection (Clostridioides difficile) in your intestines. Call your healthcare provider right away if you have watery stools, stomach pain, or fever that does not go away.
- Bone fractures (hip, wrist, or spine). Bone fractures in the hip, wrist, or spine may happen in people who take multiple daily doses of another type of medicine that reduces acid in your stomach known as proton pump inhibitors (PPI medicines) for a long period of time (a year or longer). Tell your healthcare provider if you have a bone fracture, especially in the hip, wrist, or spine.
- Severe skin reactions.VOQUEZNA can cause rare but severe skin reactions that may affect any part of your body. These serious skin reactions may need to be treated in a hospital and may be life threatening:
  - Skin rash, which may have blistering, peeling, or bleeding on any part of your skin (including your lips, eyes, mouth, nose, genital, hands, or feet).
  - You may also have fever, chills, body aches, shortness of breath, or enlarged lymph nodes.
  If you have any of these symptoms, stop taking VOQUEZNA and call your healthcare provider right away. These symptoms may be the first sign of a severe skin reaction.
- Low Vitamin B-12 levels. VOQUEZNA lowers the amount of acid in your stomach. Stomach acid is needed to absorb Vitamin B12 properly. Tell your healthcare provider if you have symptoms of low vitamin B12 levels, including irregular heartbeat, shortness of breath, lightheadedness, tingling or numbness in the arms and legs, muscle weakness, pale skin, feeling tired, or mood changes. Talk with your healthcare provider about the risk of low Vitamin B12 levels if you have been on VOQUEZNA for a long time.
- Low magnesium levels in the body can happen in people who take VOQUEZNA. Tell your healthcare provider right away if you have symptoms of low magnesium levels, including seizures, dizziness, irregular heartbeat, jitteriness, muscle aches or weakness, or spasms of the hands, feet, or voice.
- Stomach growths (fundic gland polyps). A certain type of stomach growth called fundic gland polyps may happen in people who take VOQUEZNA for a long time (more than a year). Talk with your healthcare provider about the risk of fundic gland polyps if you have been on VOQUEZNA for a long time.

The most common side effects of VOQUEZNA for treatment of erosive esophagitis or relief of heartburn related to gastroesophageal reflux disease include:

- stomach inflammation
- diarrhea
- stomach bloating
- stomach pain
- nausea

- indigestion
- constipation
- high blood pressure
- urinary tract infection

The most common side effects of VOQUEZNA when used with antibiotics for treatment of H. pylori infection include:

- diarrhea
- temporary changes in sense of taste
- vaginal yeast infection
- stomach pain

- headache
- high blood pressure
- cold-like symptoms

These are not all the possible side effects of VOQUEZNA.
For more information, ask your healthcare provider or pharmacist. Call your doctor for medical advice about side effects. You may report side effects to FDA at 1-800-FDA-1088.

How should I store VOQUEZNA?

- Store VOQUEZNA at room temperature between 68°F to 77°F (20°C to 25°C).

Keep VOQUEZNA and all medicines out of the reach of children.

General information about the safe and effective use of VOQUEZNA.
Medicines are sometimes prescribed for purposes other than those listed in a Patient Information leaflet. Do not use VOQUEZNA for a condition for which it was not prescribed. Do not give VOQUEZNA to other people, even if they have the same symptoms you have. It may harm them.
You can ask your healthcare provider or pharmacist for information about VOQUEZNA that is written for health professionals.

What are the ingredients of VOQUEZNA?
Active ingredient: vonoprazan
Inactive ingredients: ascorbic acid, croscarmellose sodium, ferric oxide red (only in 20 mg tablets), ferric oxide yellow (only in 10 mg tablets), fumaric acid, hydroxypropyl cellulose, hypromellose, magnesium stearate, mannitol, microcrystalline cellulose, polyethylene glycol 8000, and titanium dioxide.

VOQUEZNA is manufactured for and distributed by:
Phathom Pharmaceuticals, Inc.
Buffalo Grove, IL 60089, U.S.A.
VOQUEZNA, the VOQUEZNA logo, and Phathom Pharmaceuticals are registered trademarks of Phathom Pharmaceuticals, Inc.
© 2025 Phathom Pharmaceuticals, Inc. All rights reserved.

This Patient Information has been approved by the U.S. Food and Drug Administration.

Revised: 11/2025

PRINCIPAL DISPLAY PANEL - 10 mg Tablet Bottle Label

NDC 81520-100-30
30 Tablets
Rx only

VOQUEZNA®
(vonoprazan) tablets

10 mg*

For oral use

PRINCIPAL DISPLAY PANEL - 20 mg Tablet Bottle Label

NDC 81520-200-30
30 Tablets
Rx only

VOQUEZNA®
(vonoprazan) tablets

20 mg*

For oral use